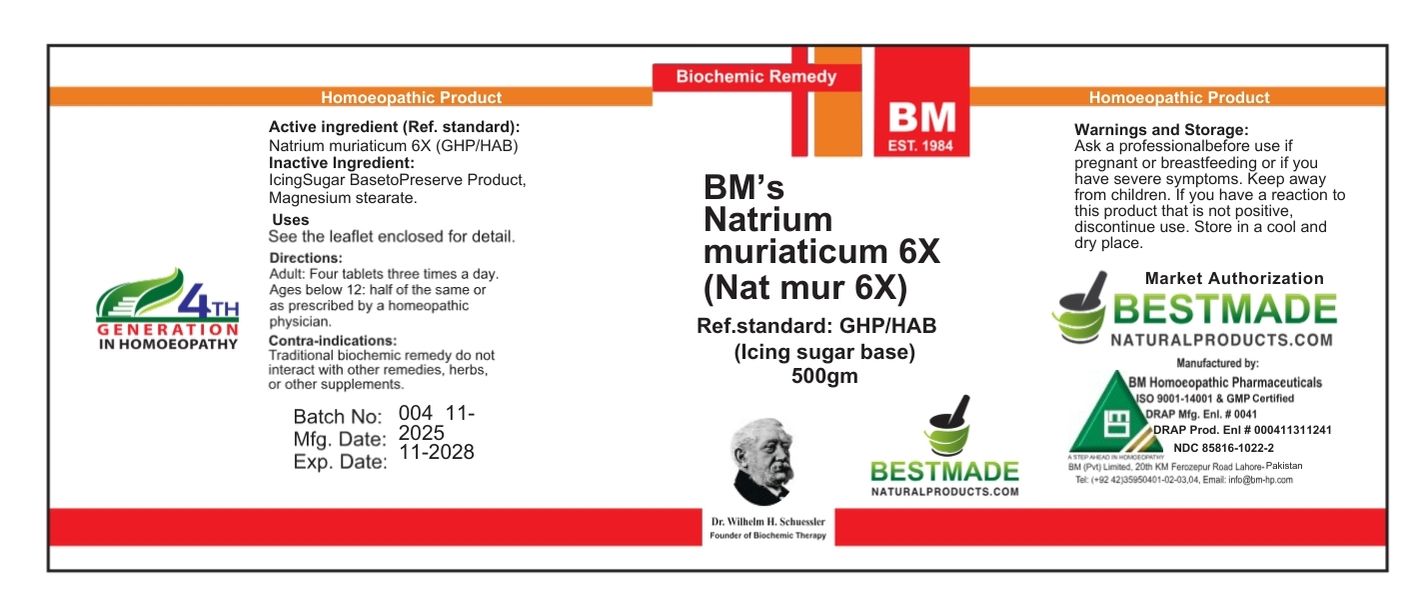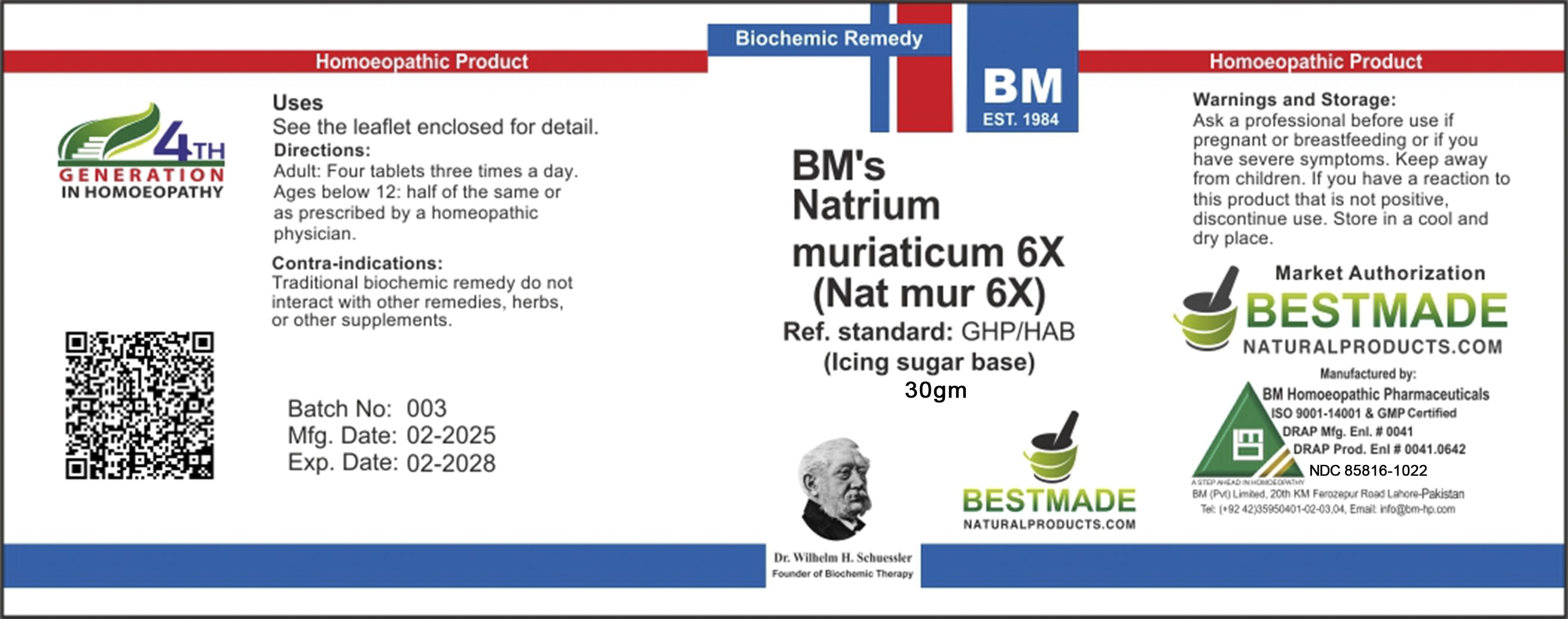 DRUG LABEL: BM Nat Mur Icing Sugar
NDC: 85816-1022 | Form: TABLET
Manufacturer: BM Private Limited
Category: homeopathic | Type: HUMAN OTC DRUG LABEL
Date: 20251202

ACTIVE INGREDIENTS: SODIUM CHLORIDE 6 [hp_X]/60 mg
INACTIVE INGREDIENTS: MAGNESIUM STEARATE 0.12 mg/60 mg; SUCROSE 58.86 mg/60 mg; SILICON DIOXIDE 0.06 mg/60 mg; GELATIN 0.9 mg/60 mg

BM nat mur 6x icing sugar

Uses
See the leaflet enclosed for detail.

Uses
See the leaflet enclosed for detail.

Directions:
Adult: Four tablets three times a day.
Ages below 12: half of the same or as prescribed by a homeopathic physician.

KEEP OUT OF REACH OF CHILDREN

Warnings and Storage:

Ask a professional before use if pregnant or breastfeeding or if you have severe symptoms. Keep away from children. If you have a reaction to this product that is not positive, discontinue use. Store in a cool and dry place.

Warnings and Storage:

Ask a professional before use if pregnant or breastfeeding or if you have severe symptoms. Keep away from children. If you have a reaction to this product that is not positive, discontinue use. Store in a cool and dry place.

INACTIVE INGREDIENT

Inactive Ingredients: Sucrose, Gelatine, Magnesium Stearate, Silicon Dioxide

Active Ingredient: Natrum Muriaticum

CONTRAINDICATIONS

Contra-indications:
Traditional biochemic remedy do not interact with other remedies, herbs, or other supplements.

Package 1 (30g)

Package 2 (500g)